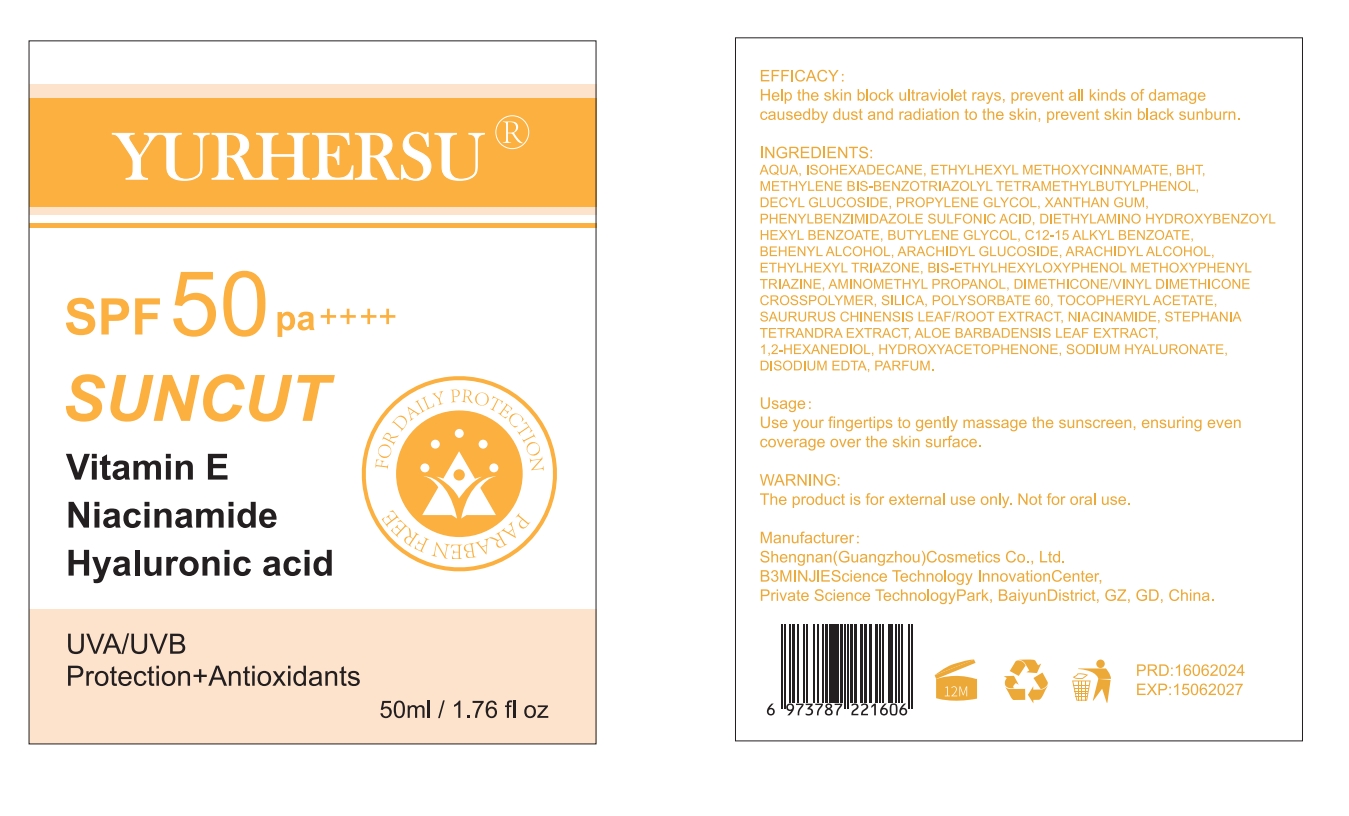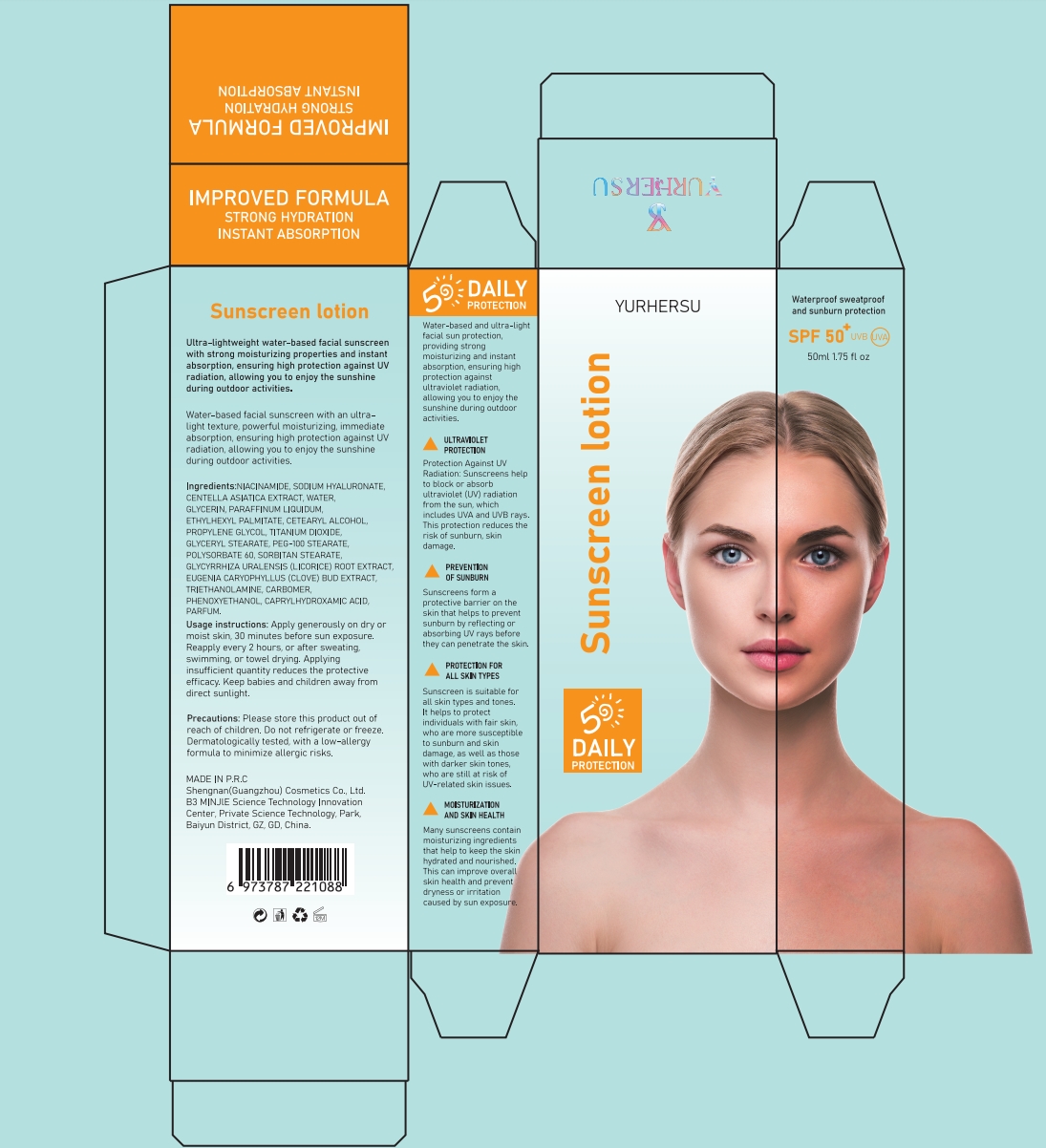 DRUG LABEL: YURHERSU SUNCUT
NDC: 84019-003 | Form: LOTION
Manufacturer: Shengnan (Guangzhou) Cosmetics Co., LTD
Category: otc | Type: HUMAN OTC DRUG LABEL
Date: 20240629

ACTIVE INGREDIENTS: ETHYLHEXYL TRIAZONE 100 mg/1 g
INACTIVE INGREDIENTS: DECYL GLUCOSIDE; BUTYLATED HYDROXYTOLUENE; WATER; ISOHEXADECANE

YURHERSU SUNCUT

Active ingredients

ETHYLHEXYL METHOXYCINNAMATE 1%
METHYLENE BIS-BENZOTRIAZOLYL TETRAMETHYLBUTYLPHENOL 1%
PHENYLBENZIMIDAZOLE SULFONIC ACID 0.5%
ETHYLHEXYL TRIAZONE 0.5%
BIS-ETHYLHEXYLOXYPHENOL METHOXYPHENYL TRIAZINE 0.5%

PURPOSE SECTION

Help the skin block ultraviolet rays, prevent all kinds of damagecausedby dust and radiation to the skin, prevent skin black sunburn.

WARNINGS

The product is for external use only. Not for oral use.

Stop use and ask a doctor if

rash occurs

Do not use

on damaged or broken skin

When using this product

keep out of eyes. Rinse with water to remove

Keep out of reach of children.

If swallowed, get medical help or contact a Poison Control Center right away.

For sunscreen use

apply liberally 15 minutes before sun exposure
reapply at least every 2 hours

Uses

Apply appropriate dermatitis cream amount to desired areasand massage until fully absorbed. Tiwvice a day.

INACTIVE INGREDIENT

AQUA,ISOHEXADECANE,BHT,DECYL GLUCOSIDE,PROPYLENE GLYCOL,XANTHAN GUM,DIETHYLAMINO HYDROXYBENZOYL HEXYL BENZOATE,BUTYLENE GLYCOL,C12-15 ALKYL BENZOATE,BEHENYL ALCOHOL,ARACHIDYL GLUCOSIDE,ARACHIDYL ALCOHOL,AMINOMETHYL PROPANOL,DIMETHICONE/VINYL DIMETHICONE CROSSPOLYMER,SILICA,POLYSORBATE 60,TOCOPHERYL ACETATE,SAURURUS CHINENSIS LEAF/ROOT EXTRACT,TARAXACUM OFFICINALE (DANDELION) LEAF EXTRACT,STEPHANIA TETRANDRA EXTRACT,ALOE BARBADENSIS LEAF EXTRACT,
1,2-HEXANEDIOL,HYDROXYACETOPHENONE,SODIUM HYALURONATE.DISODIUM EDTA,PARFUM.